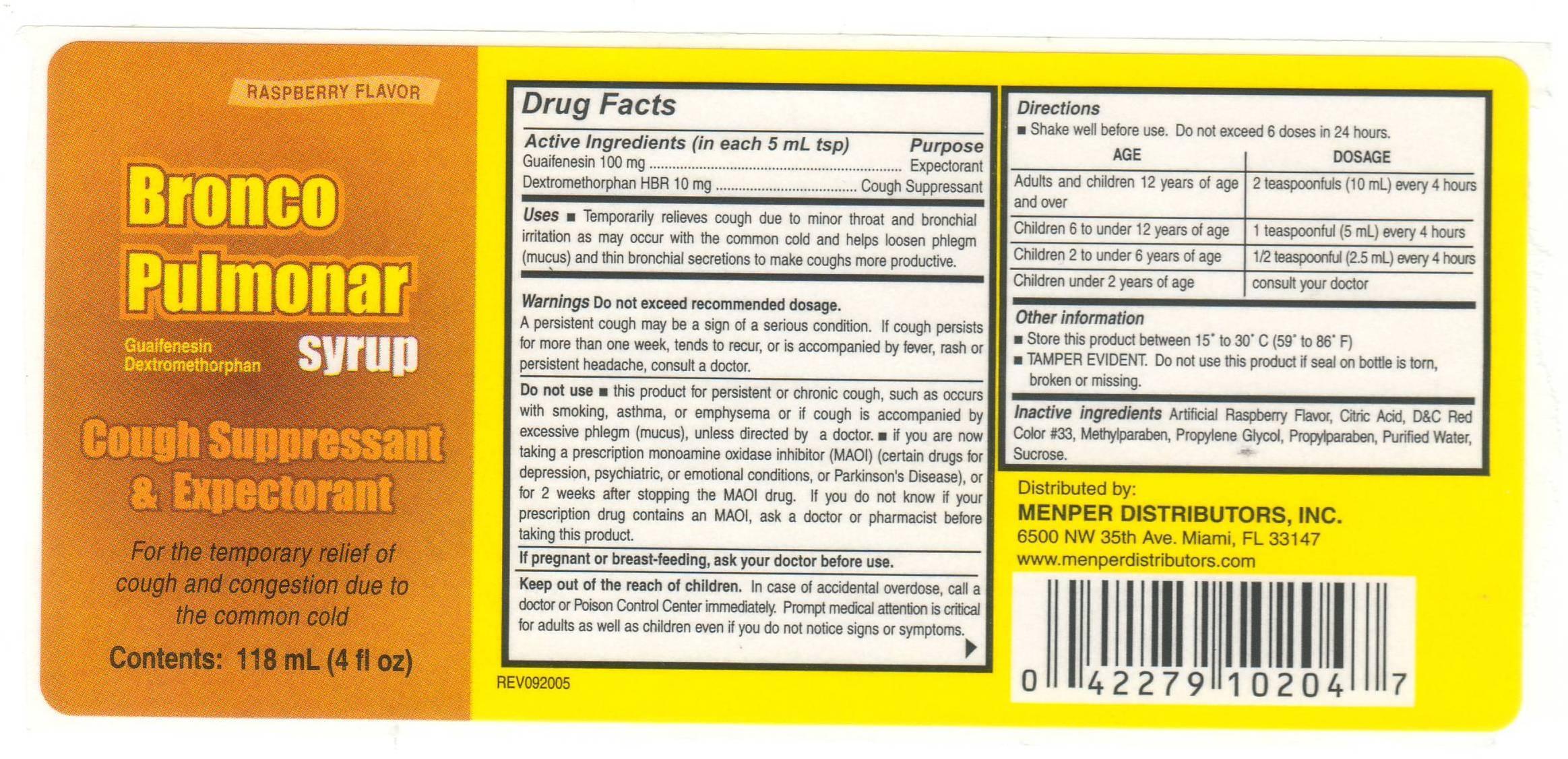 DRUG LABEL: Bronco Pulmonar Syrup
NDC: 53145-030 | Form: LIQUID
Manufacturer: Menper Distributors, Inc.
Category: otc | Type: HUMAN OTC DRUG LABEL
Date: 20130829

ACTIVE INGREDIENTS: GUAIFENESIN 100 mg/5 mL; DEXTROMETHORPHAN HYDROBROMIDE 10 mg/5 mL
INACTIVE INGREDIENTS: RASPBERRY; CITRIC ACID ACETATE; D&C RED NO. 33; METHYLPARABEN; PROPYLENE GLYCOL; PROPYLPARABEN; WATER; SUCROSE

Active ingredients (in each 5mL tsp)

Guaifenesin 100 mg………………………………Expectorant

Dextromethorphan HBr 10 mg…………………….Cough suppressant

PURPOSE

Expectorant

Cough Suppressant

Uses

- Temporarily relieves cough due to minor throat and bronchial irritation and nasal congestion as may occur with the common cold or inhaled irritants

Warnings Do not exceed recommended dosage.

- A persistent cough may be a sign of a serious condition. If cough persists more than one week, tends to reoccur, or is accompanied by fever, rash, or persistent headache, consult a doctor.

Do not use:

- This product for persistent or chronic cough, such as occurs with smoking, asthma, or emphysema or if cough is accompanied by excessive phlegm (mucus), unless directed by a doctor.
- if you are now taking a prescription monoamine oxidase inhibitor (MAOI) (certain drugs for depression, psychiatric or emotional conditions, or Parkinson’s disease), or for 2 weeks after stopping the MAOI drug. If you do not know if your prescription drug contains an MAOI, ask a doctor or pharmacist before taking this product.

Keep out of reach of children.

PREGNANCY OR BREAST FEEDING

If you are pregnant or breast-feeding, ask a health professional before use.

In case of accidental overdose, get medical help or contact a Poison Control Center right away.

Directions

- Do not exceed 6 doses in 24 hours.

age dose

Adults and children 2 teaspoonfuls (10 mL)

12 years of age and over....................................... every 4 hours

Children 6 to under 1 teaspoonful (5 mL)

12 years of age..................................................... every 4 hours

Children 2 to under 1/2 teaspoonful (2.5 mL)

6 years of age....................................................... every 4 hours

Children under 2 years of age.................................. consult your doctor

Other information

- Store this product between 15°-30°C (59°-86°F)
- TAMPER EVIDENT. Do not use this product if seal on bottle is torn, broken or missing.

INACTIVE INGREDIENT

Inactive ingredients Artificial Raspberry Flavor, Citric Acid, D&C red #33, Methylparaben, Propylene Glycol, Propylparaben , Purified Water, Sucrose